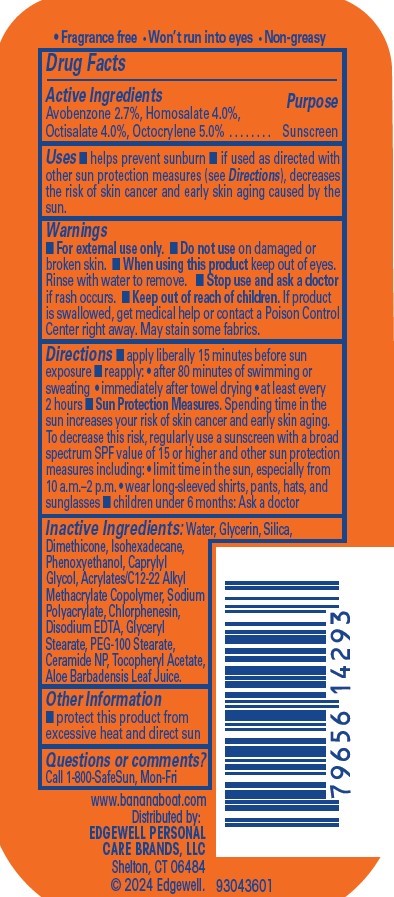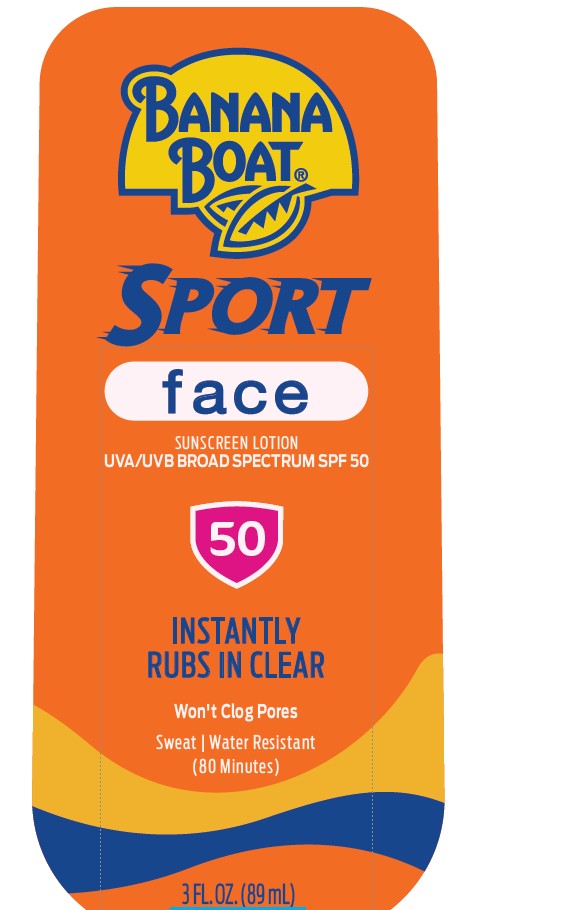 DRUG LABEL: Banana Boat
NDC: 63354-773 | Form: LOTION
Manufacturer: Edgewell Personal Care Brands LLC
Category: otc | Type: HUMAN OTC DRUG LABEL
Date: 20240715

ACTIVE INGREDIENTS: HOMOSALATE 4 g/100 g; AVOBENZONE 2.7 g/100 g; OCTISALATE 4 g/100 g; OCTOCRYLENE 5 g/100 g
INACTIVE INGREDIENTS: PEG-100 STEARATE; ALOE VERA LEAF; WATER; SODIUM POLYACRYLATE (2500000 MW); GLYCERYL MONOSTEARATE; ISOHEXADECANE; EDETATE DISODIUM; GLYCERIN; SILICON DIOXIDE; DIMETHICONE; PHENOXYETHANOL; CAPRYLYL GLYCOL; CERAMIDE NP; .ALPHA.-TOCOPHEROL ACETATE; CHLORPHENESIN

Active Ingredients

Avobenzone 2.7%, Homosalate 4.0%, Octisalate 4.0%, Octocrylene 5.0%

Purpose

Sunscreen

Uses

• helps prevent sunburn • if used as directed with other sun protection measures (see Directions), decreases the risk of skin cancer and early skin aging caused by the sun.

Warnings

For external use only.

May stain some fabrics.

Do not use

on damaged or broken skin.

When using this product

keep out of eyes. Rinse with water to remove.

Stop use and ask a doctor

if rash occurs.

Keep out of reach of children.

If product is swallowed, get medical help or contact a Poison Control Center right away.

Directions

• apply liberally 15 minutes before sun exposure reapply: • after 80 minutes of swimming or sweating • immediately after towel drying • at least every 2 hours Sun Protection Measures. Spending time in the sun increases your risk of skin cancer and early skin aging. To decrease this risk, regularly use a sunscreen with a broad spectrum SPF value of 15 or higher and other sun protection measures including: • limit time in the sun, especially from 10 a.m.–2 p.m. • wear long-sleeved shirts, pants, hats, and sunglasses children under 6 months: Ask a doctor

Inactive Ingredients

Water, Glycerin, Silica, Dimethicone, Isohexadecane, Phenoxyethanol, Caprylyl Glycol, Acrylates/C12-22 Alkyl Methacrylate Copolymer, Sodium Polyacrylate, Chlorphenesin, Disodium EDTA, Glyceryl Stearate, PEG-100 Stearate, Ceramide NP, Tocopheryl Acetate, Aloe Barbadensis Leaf Juice.

Other Information

protect this product from excessive heat and direct sun

Questions or comments?

Call 1-800-SafeSun, Mon-Fri

PACKAGE LABEL

BANANA BOAT
SPORT
face
SUNSCREEN LOTION
UVA/UVB BROAD SPECTRUM SPF 50
50
INSTANTLY
RUBS IN CLEAR
Won't Clog Pores
Sweat | Water Resistant (80 Minutes)
3 FL. OZ. (89 mL)